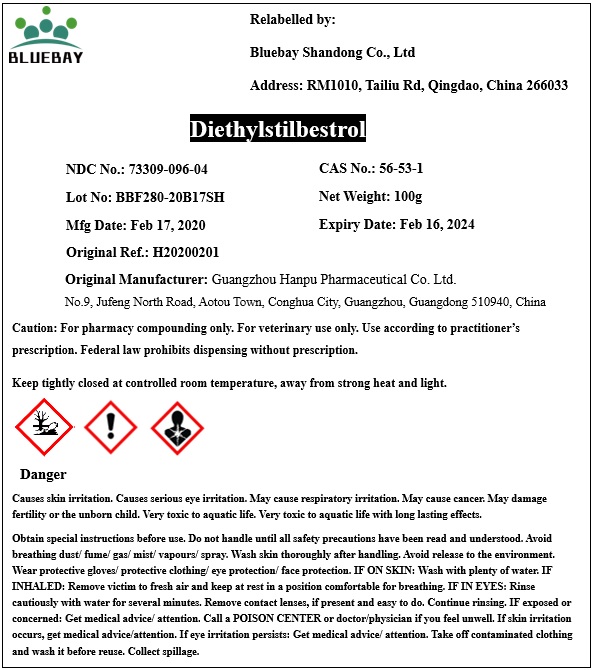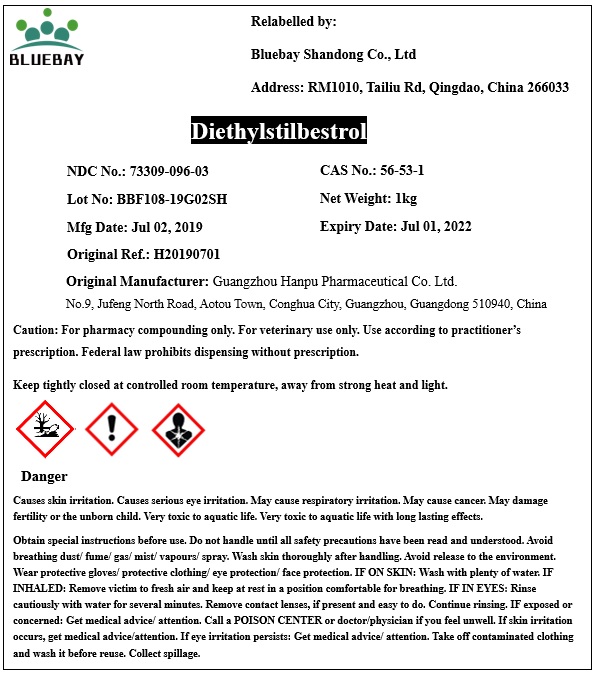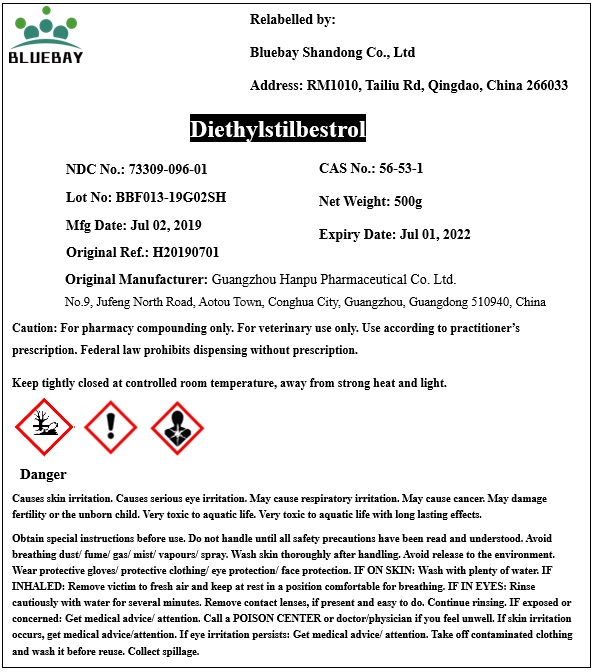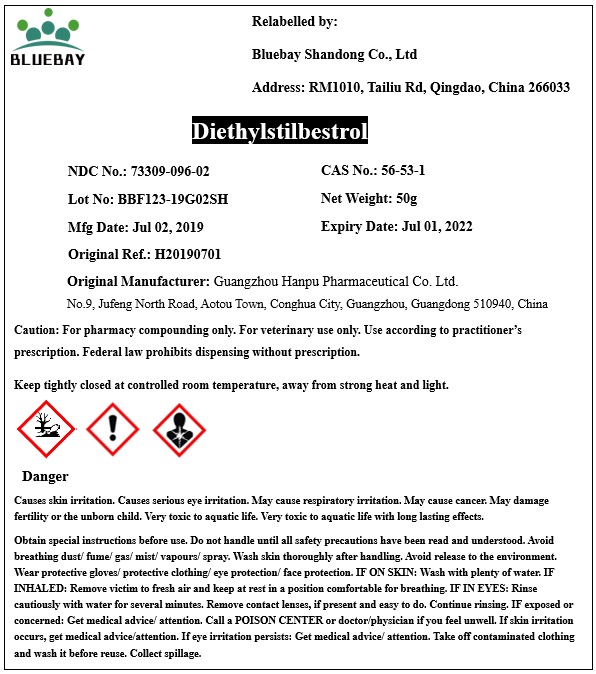 DRUG LABEL: Diethylstilbestrol
NDC: 73309-096 | Form: POWDER
Manufacturer: BLUEBAY SHANDONG CO.,LTD
Category: other | Type: BULK INGREDIENT
Date: 20200625

ACTIVE INGREDIENTS: DIETHYLSTILBESTROL 1 g/1 g

Diethylstilbestrol